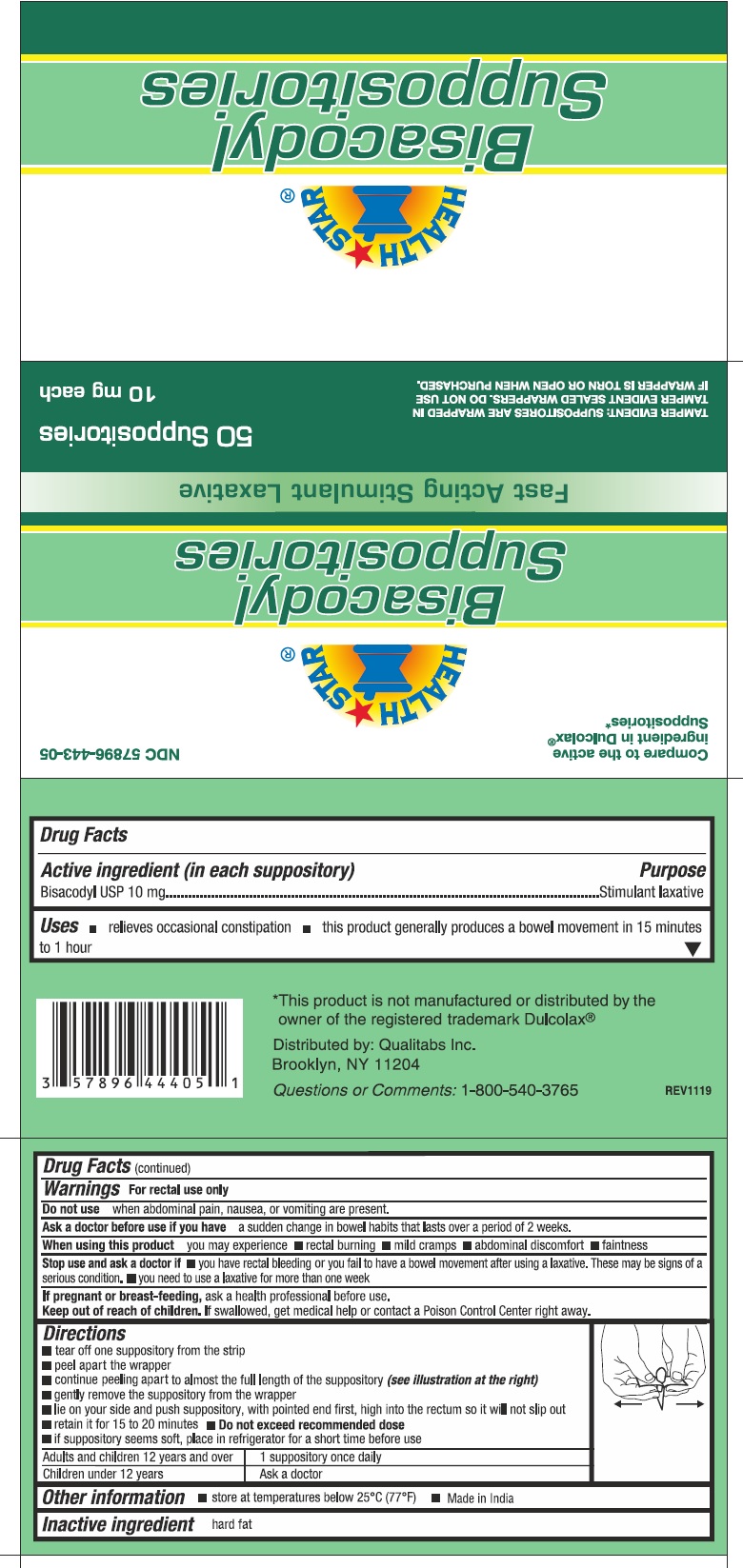 DRUG LABEL: Bisacodyl
NDC: 57896-443 | Form: SUPPOSITORY
Manufacturer: GERI-CARE PHARMACEUTICAL CORP
Category: otc | Type: HUMAN OTC DRUG LABEL
Date: 20251023

ACTIVE INGREDIENTS: BISACODYL 10 mg/1 1
INACTIVE INGREDIENTS: FAT, HARD

Bisacodyl Suppositories 443

Drug Facts

Active ingredient (in each suppository)

Bisacodyl USP, 10 mg

Purpose

Stimulant Laxative

Uses

- relieves occasional constipation
- this product generally produces a bowel movement in 15 minutes to 1 hour

Warnings

For rectal use only

Do not use

when abdominal pain, nausea, or vomiting are present.

Ask a doctor before use if you have a sudden change in bowel habits that lasts over a period 2 weeks.

When using this product you may experience

- rectal burning
- mild cramps
- abdominal discomfort
- faintness

Stop use and ask a doctor if

- you have rectal bleeding or you fail to have bowel movement after using a laxative. These may be signs of a serious condition.
- you need to use a laxative product for more than one week

PREGNANCY OR BREAST FEEDING

If pregnant or breast-feeding, ask a health professional before use.

Keep out of reach of children. If swallowed, get medical help or contact a Poison Control Center right away.

Directions

- tear off one suppository from the strip
- peel apart the wrapper
- continue peeling apart to almost the full length of the suppository (see illustration at the right)
- gently remove the suppository from the wrapper
- lie on your side and push suppository, with pointed end first, high into the rectum so it will not slip out
- retain it for about 15 to 20 minutes.
- Do not exceed recommended dose
- if suppository seems soft, place in refrigerator for a short time before use

adults and children 12 years and over | 1 suppository once daily
children under 12 years | Ask a doctor

Other information

- store at temperatures below 25 C (77F)
- Made in India

Inactive ingredient hard fat

Questions or Comments? 1-800-540-3765